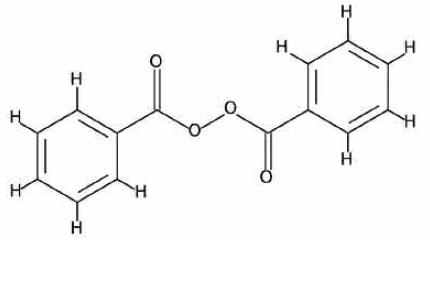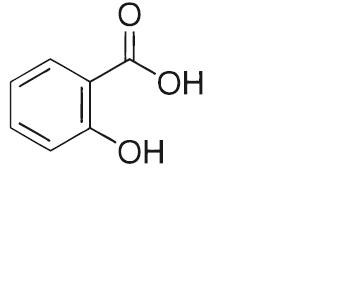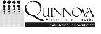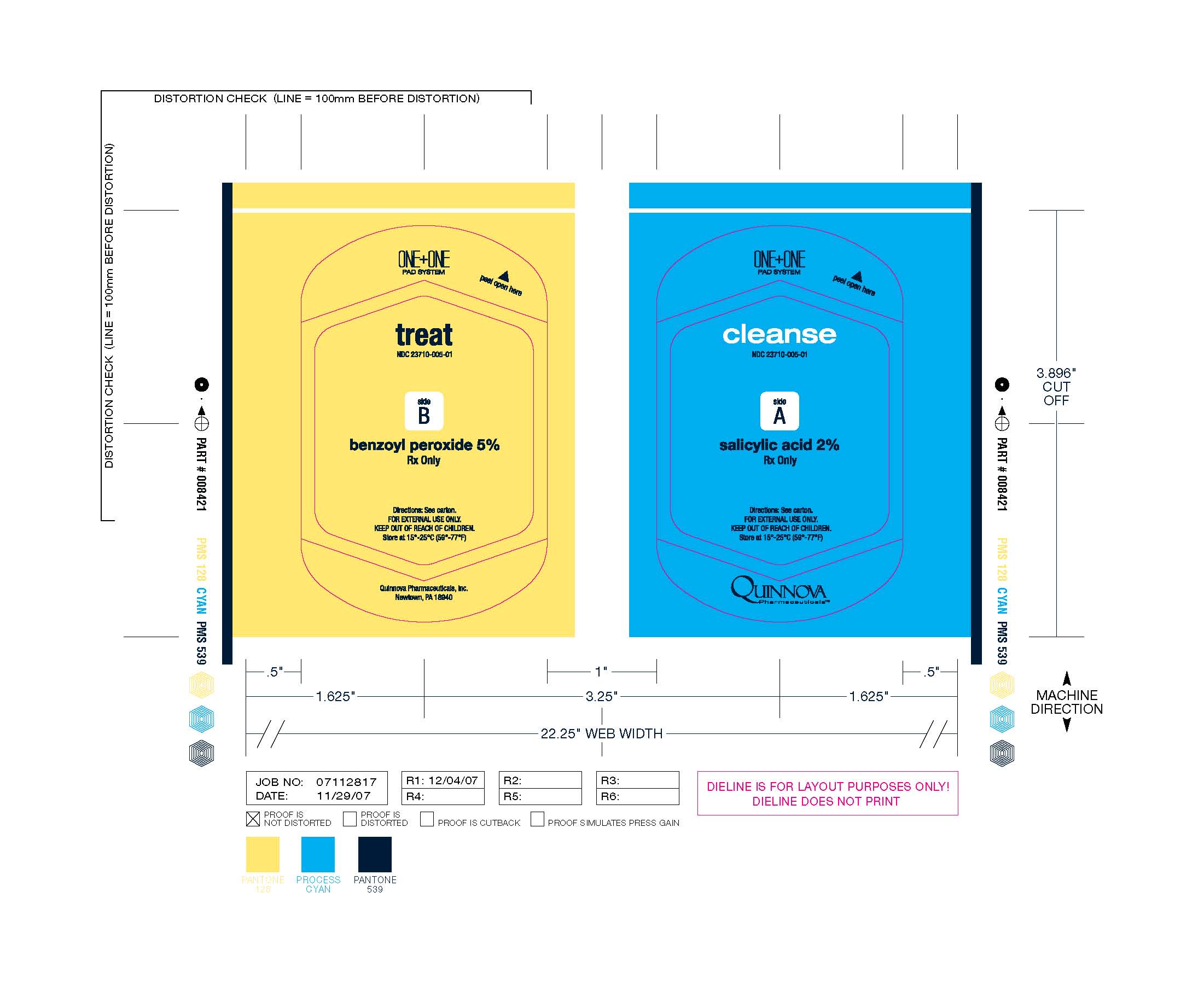 DRUG LABEL: Clease and Treat
NDC: 23710-052 | Form: CLOTH
Manufacturer: Quinnova Pharmaceuticals, Inc.
Category: other | Type: NON-STANDARDIZED ALLERGENIC LABEL
Date: 20091211

ACTIVE INGREDIENTS: BENZOYL PEROXIDE 0.8 g/5 g; SELENIUM SULFIDE 0.5 g/5 g
INACTIVE INGREDIENTS: AMMONIUM LAURYL SULFATE; CARBOMER 934; GLYCERIN; METHYLPARABEN; PROPYLENE GLYCOL; PROPYLPARABEN; WATER; SODIUM CHLORIDE; SODIUM HYDROXIDE; AMMONIUM LAURYL SULFATE; POWDERED CELLULOSE; GLYCERYL RICINOLEATE; TRISODIUM CITRATE DIHYDRATE

CLEANSE AND TREAT

DESCRIPTION

Cleanse & Treat
(benzoyl peroxide pad and salicylic acid pad)
Rx Only

Cleanse & Treat contains two separate and distinct non-woven pads enclosed in a heat-sealed foil pack compartmentalized from one another within the foil pack by filmstock. One non-woven pad bears a preparation consisting of 5% benzoyl peroxide and the following inactive ingredients: ammonium lauryl sulfate, carbomer, disodium cocoamphodiacetate, DMDM hydantoin, glycerin, methylparaben, propylene glycol, propylparaben, purified water, sodium chloride, sodium hydroxide. The other non-woven pad bears a preparation consisting of 2% salicylic acid and the following inactive ingredients: ammonium lauryl sulfate, cellulose gum, disodium ricinoleamido MEA-sulfosuccinate, DMDM hydantoin, propylene glycol monoricinoleate, purified water, sodium citrate dihydrate.

CHEMICAL STRUCTURE

Benzoyl peroxide is an oxidizing agent that possesses antibacterial properties and is classified as a keratolytic. It has an empirical formula of C14H10O4 with a molecular weight of 242.23. Benzoyl peroxide has the following molecular structure:

Salicylic acid is the 2 hydroxy derivative of benzoic aid. It has an empirical formula of C7H6O3 with a molecular weight of 138.12. Salicylic acid has the following molecular structure:

CLINICAL PHARMACOLOGY

The exact method of action of benzoyl peroxide in acne vulgaris is not known, however, its antibacterial activity against Propionibacterium acnes, together with its mild keratolytic effect, is believed to be its significant mode of action.

PEDIATRIC USE

Pediatric Use - Cleanse & Treat should not be used by children under 12 years of age.

PATIENT COUNSELING INFORMATION

Information for Patients - Patients should avoid unnecessary sun exposure and use a sunscreen when in sunlight. Contact with hair, fabrics, or any colored materials may result in bleaching or discoloration. Patients should avoid concomitant use of other drugs that may contribute to elevated serum salicylate levels where the potential for toxicity exists. Symptoms of salicylate toxicity may include nausea, vomiting, dizziness, loss of hearing, tinnitus, lethargy, hyperpnea and diarrhea. In the event of salicylate toxicity, the use of Cleanse & Treat should be discontinued, fluids should be administered to promote urinary excretion and medical assistance should be obtained immediately.

Carcinogenesis, Mutagenesis, Impairment of Fertility - Data from some studies using a strain of mice highly susceptible to eveloping cancer suggest that benzoyl peroxide acts as a tumor promoter. The clinical significance of these findings to humans is not known. Benzoyl peroxide has not been found to be mutagenic in the Ames Salmonella Test and there are no published data suggesting that it impairs fertility. No data are available concerning potential carcinogenic or reproductive effects of salicylic acid. It has not been found to be mutagenic in the Ames Salmonella Test and there are no published data suggesting that it impairs fertility.

PREGNANCY

Pregnancy (Category C) - Animal reproduction studies have not been performed with benzoyl peroxide and it is not known whether benzoyl peroxide can cause fetal harm when administered to a pregnant woman. Nevertheless, benzoyl peroxide should be used by a pregnant woman only if necessary. Salicylic acid has been shown to be teratogenic in rats and monkeys. It is difficult to extrapolate from oral doses of acetylsalicylic acid used in these studies to topical administration as the oral dose to monkeys may represent 10 times or more the maximum daily human dose of salicylic acid when applied topically as directed with Cleanse &Treat. There are no adequate and well-controlled studies in pregnant women. Nevertheless, salicylic acid should be used by a pregnant woman only if necessary.

INDICATIONS AND USAGE

Cleanse & Treat is indicated for the topical treatment of acne vulgaris.

CONTRAINDICATIONS

Cleanse & Treat is contraindicated in patients with a history of hypersensitivity to any of its ingredients.

ADVERSE REACTIONS

Allergic contact dermatitis and/or dryness have been reported with topical benzoyl peroxide and salicylic acid, both when used separately and in combination with one another.

OVERDOSAGE

If excessive scaling, erythema or edema occurs, patients should discontinue use of Cleanse & Treat and consult with their physician.

DOSAGE AND ADMINISTRATION

Unless otherwise directed by a prescribing physician, patients should apply one salicylic acid pad and one benzoyl peroxide pad to affected areas twice per day. Cleanse & Treat is a leave-on acne treatment, intended for use without water or additional cleansers unless otherwise directed by your physician.

HOW SUPPLIED

Each Cleanse & Treat packette consists of one 0.8 g. 5% benzoyl peroxide pad and one 0.5 g. 2% salicylic acid pad, with each pad separated from one another by filmstock and both pads enclosed together in an individual heat-sealed foil pack bearing the NDC Number 23710-052-02.

Store at 15°-25° C (59°-77° F)

REFERENCES

Cleanse & Treat covered by US Patents: 5,254,109; 5,417,674; and 5,562,642.

Quinnova Pharmaceuticals, Inc., Newtown, PA 18940, (877) 660-6263, www.QUINNOVA.com.

Prescribing Information as of April 2008.

CLNSTR011 4/08